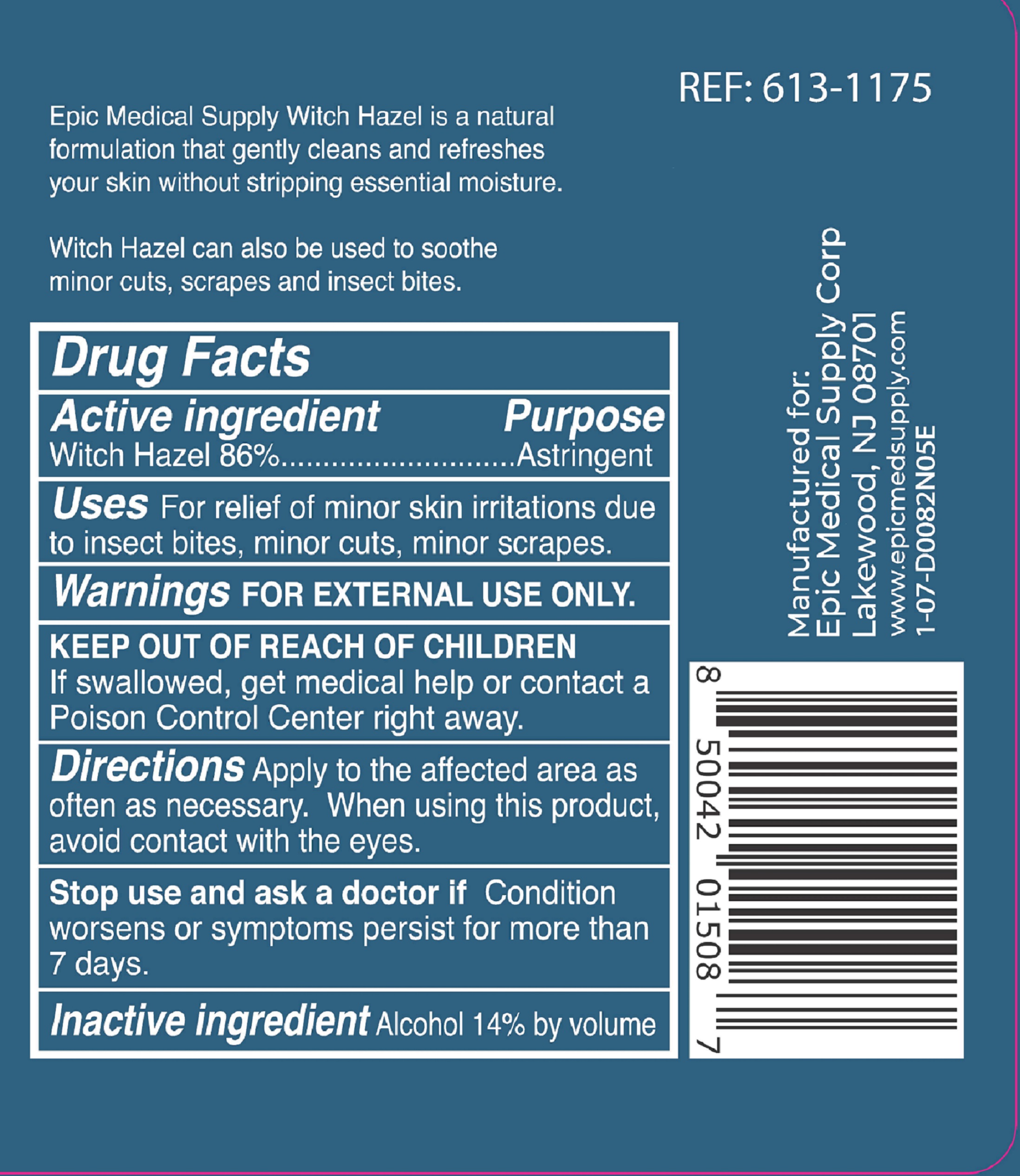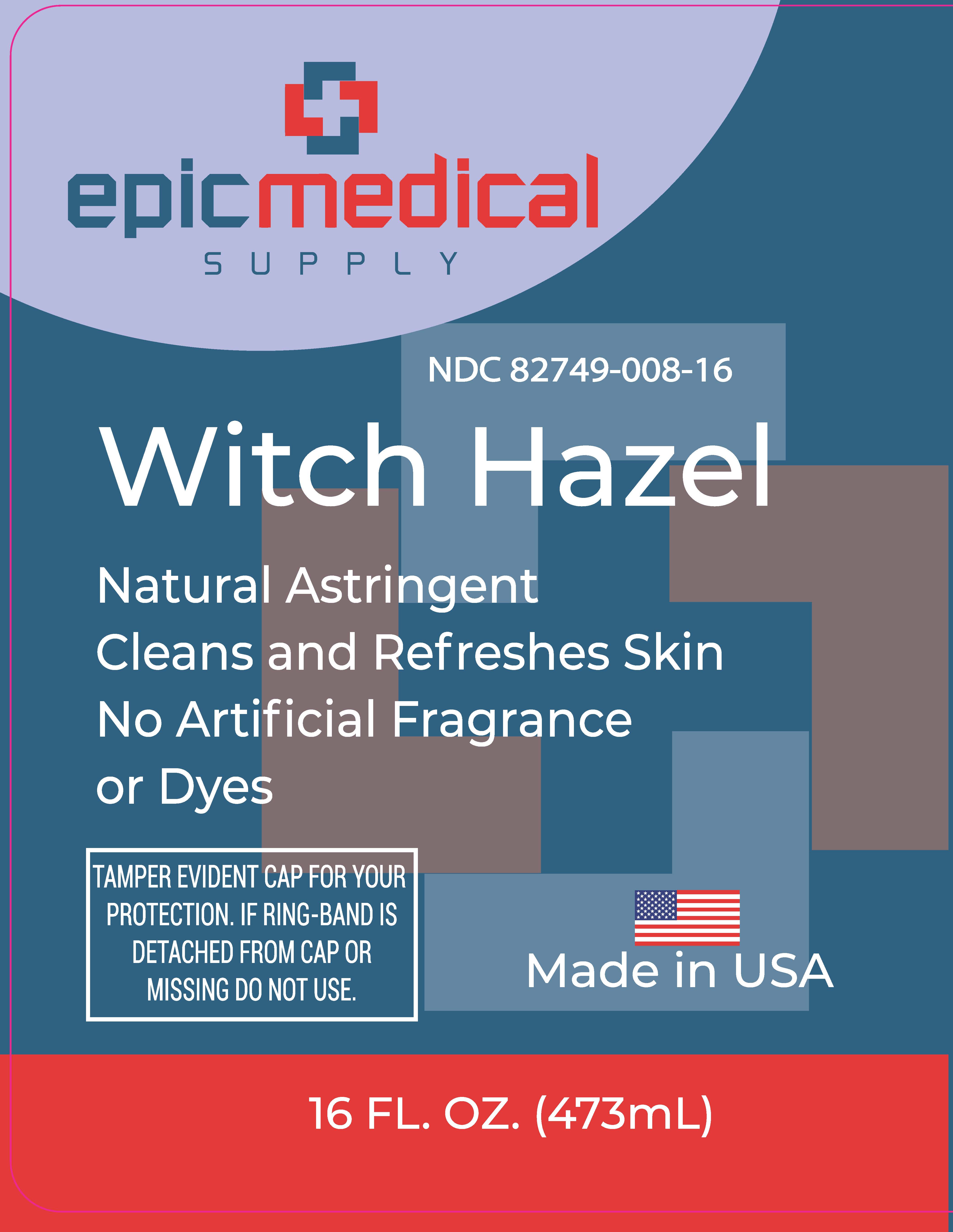 DRUG LABEL: Witch Hazel
NDC: 82749-008 | Form: LIQUID
Manufacturer: Epic Medical Supply Corp.
Category: otc | Type: HUMAN OTC DRUG LABEL
Date: 20241120

ACTIVE INGREDIENTS: WITCH HAZEL 86 mg/100 mL
INACTIVE INGREDIENTS: ALCOHOL

Witch Hazel

Active Ingredient

Witch Hazel 86%

Purpose

Astringent

Uses: Relieves minor skin irritation due to:

- insect bites
- minor cuts
- minor scrapes

Warnings

For external use only

When using this product

- Avoid contact with eyes. If contact occurs, rinse thoroughly with water.

Stop use and ask a doctor if

- Condition worsens or symptoms persist for more than 7 days.

Keep out of reach of children.

- If swallowed, get medical help or contact a Poison Control Center right away.

Directions

- After cleansing apply generously to cotton ball and gently wipe skin.
- Apply as often as needed.

Inactive ingredients

Alcohol 14% by volume.

Principal Display Panel

Epic Medical Supply

NDC 82749-008-16

Witch Hazel

Natural Astringent

Cleans and Refreshes Skin

No Artificial Fragrance or Dyes

TAMPER EVIDENT CAP FOR YOUR PROTECTION

IF RING-BAND IS DETACHED FROM CAP OR MISSING, DO NOT USE.

473 mL 16 fl oz.